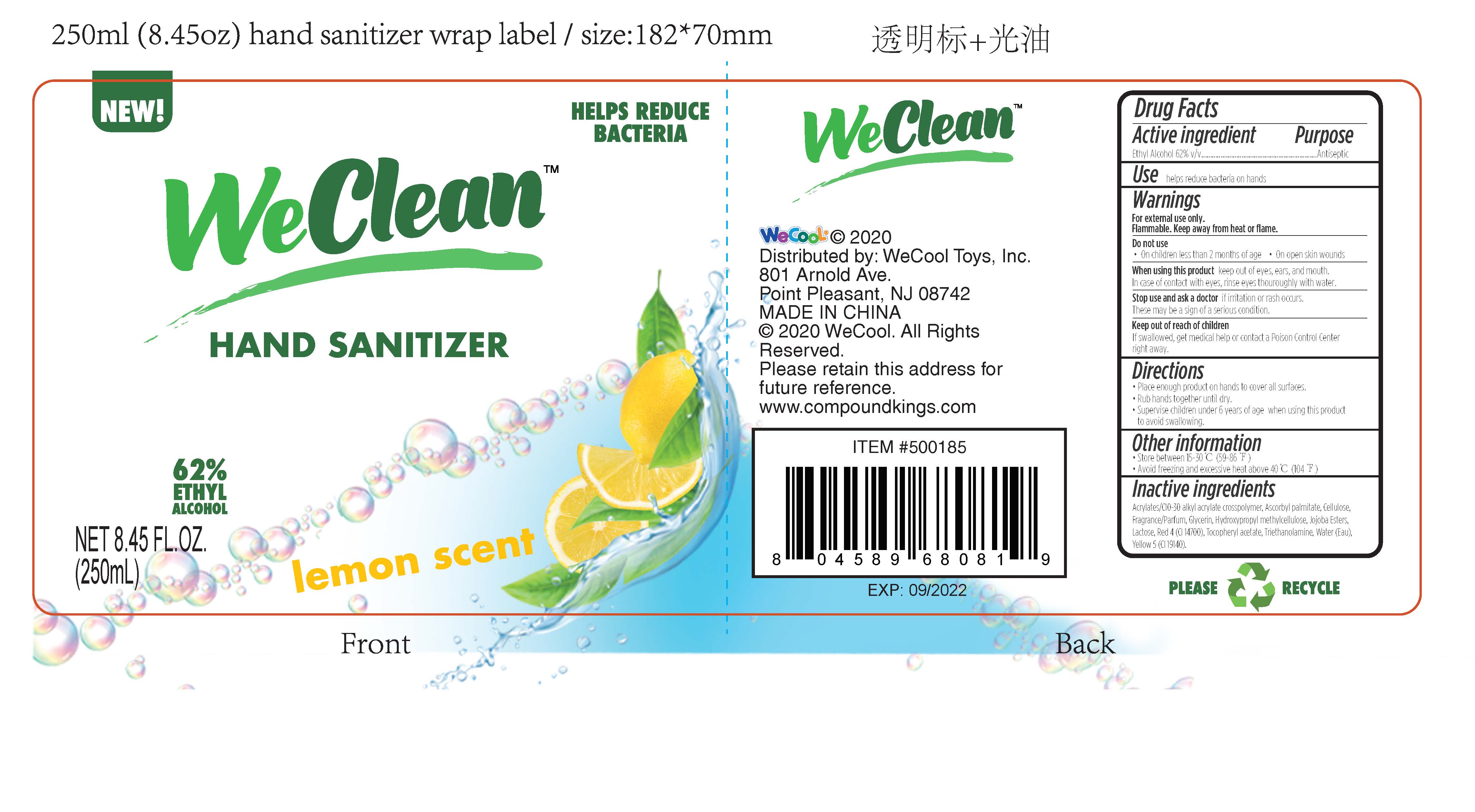 DRUG LABEL: WeClean Hand Sanitizer Lemon Scent
NDC: 51706-956 | Form: GEL
Manufacturer: Landy International
Category: otc | Type: HUMAN OTC DRUG LABEL
Date: 20220321

ACTIVE INGREDIENTS: ALCOHOL 62 mL/100 mL
INACTIVE INGREDIENTS: CARBOMER COPOLYMER TYPE A (ALLYL PENTAERYTHRITOL CROSSLINKED); ASCORBYL PALMITATE; POWDERED CELLULOSE; HYPROMELLOSES; TROLAMINE; JOJOBA OIL, RANDOMIZED; LACTOSE, UNSPECIFIED FORM; FD&C RED NO. 4; GLYCERIN; WATER; ALPHA-TOCOPHEROL ACETATE; FD&C YELLOW NO. 5

51706-956 WeClean Hand Sanitizer Lemon Scent Ethyl Alcohol(62%)

Active Ingredient(s)

Ethyl Alcohol 62%

Purpose

Antiseptic

Use

helps eliminate bacteria on hands

Warnings

For external use only.
Flammable, Keep away from heat or flame,
Do not use
On children less than 2 months of age. on open skin wounds
When using this product keep out of eyes, ear, and mouth.
In case of contact with eve, rinse eyes thouroughly with water
Stop use and ask a doctor if irritation or rash occurs,
These may be a sign of a serious condition.

Keep out of reach of children. except under adult supervision.

If swallowed, get medical help or contact a poison control center right away.

Directions

Place enough product on hands to cover all surfaces.
Rub hands together until dry.
Supervise children under 6 years of age When using this product
to avoid swallowing.

Inactive ingredients

Acrylates/C10-30 alkyl acrylate crosspolymer,Ascorbyl palmitate,Cellulose,
Fragrance/Parfum, Glycerin, Hydroxypropyl methylcellulose,Jojoba Esters,
Lactose,Red 4(Cl14700), Tocopheryl acetate,Triethanolamine,Water(Eau).
Yellow 5(C119140).